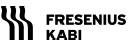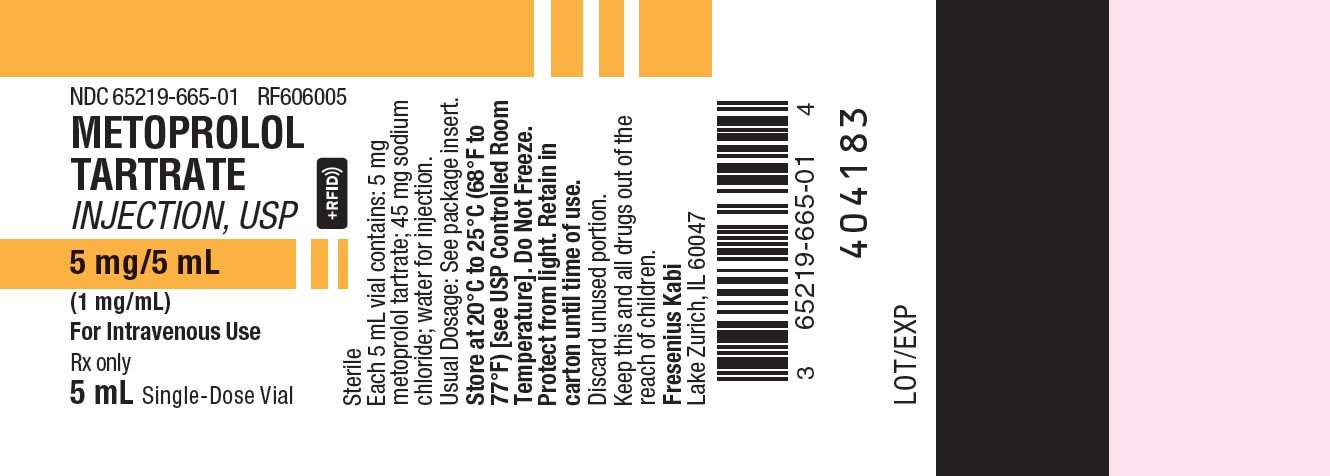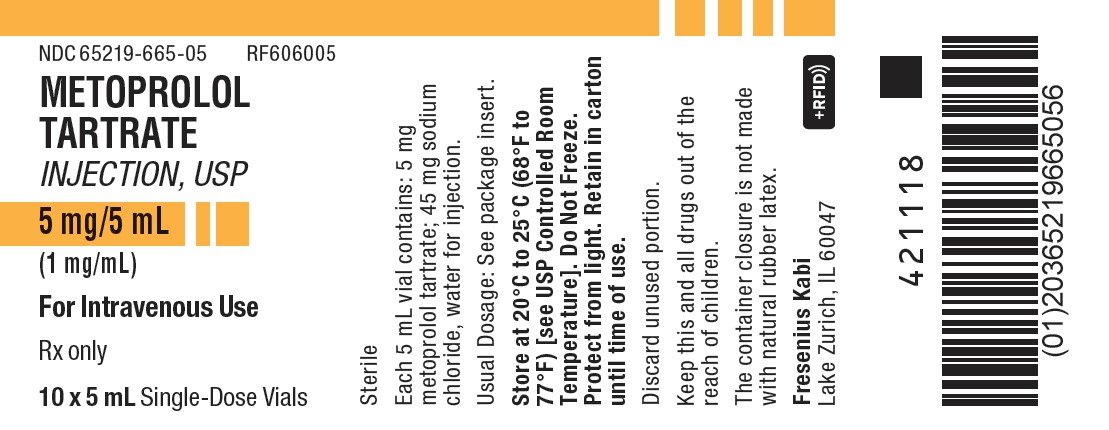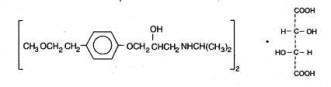 DRUG LABEL: Metoprolol
NDC: 65219-665 | Form: INJECTION, SOLUTION
Manufacturer: Fresenius Kabi USA, LLC
Category: prescription | Type: HUMAN PRESCRIPTION DRUG LABEL
Date: 20260202

ACTIVE INGREDIENTS: METOPROLOL TARTRATE 5 mg/5 mL
INACTIVE INGREDIENTS: SODIUM CHLORIDE 45 mg/5 mL; WATER 45 mg/5 mL

HIGHLIGHTS OF PRESCRIBING INFORMATION

These highlights do not include all the information needed to use METOPROLOL TARTRATE INJECTION safely and effectively. See full prescribing information for METOPROLOL TARTRATE INJECTION
METOPROLOL TARTRATE INJECTION, for intravenous use
Initial U.S. Approval: 1978

1 INDICATIONS AND USAGE

Metoprolol tartrate injection is a beta-adrenergic receptor inhibitor indicated for the treatment of definite or suspected acute myocardial infarction in hemodynamically stable patients to reduce cardiovascular mortality when used in conjunction with oral metoprolol maintenance therapy (1).

2 DOSAGE AND ADMINISTRATION

- Initiate therapy in a coronary care or similar unit immediately after the patients hemodynamic condition has stabilized (2).
- Begin treatment with an intravenous administration of three bolus injections of 5 mg each, at approximately 2-minute intervals. Monitor blood pressure, heart rate and electrocardiogram (2).
- Following administration of metoprolol tartrate injection, transition the patient to an oral formulation of metoprolol (2).

3 DOSAGE FORMS AND STRENGTHS

Injection: 5 mg metoprolol tartrate supplied in 5 mL vials (3)

4 CONTRAINDICATIONS

- Known hypersensitivity to product components. (4)
- Severe bradycardia, greater than first degree heart block, or sick sinus syndrome without a pacemaker. (4)
- Cardiogenic shock or decompensated heart failure. (4)

5 WARNINGS AND PRECAUTIONS

- Worsening cardiac failure may occur. (5.1)
- Bronchospastic Disease: Avoid beta blockers. (5.2)
- Pheochromocytoma: First initiate therapy with an alpha blocker. (5.3)
- May aggravate symptoms of arterial insufficiency. (5.4)

6 ADVERSE REACTIONS

- Most common adverse reactions: tiredness, dizziness, shortness of breath, bradycardia, hypotension, pruritus. (6.1)

To report SUSPECTED ADVERSE REACTIONS, contact Fresenius Kabi USA, LLC at 1-800-551-7176 or FDA at 1-800-FDA-1088 or www.fda.gov/medwatch.

7 DRUG INTERACTIONS

- Catecholamine-depleting drugs may have an additive effect when given with beta-blocking agents. (7.1)
- Patients may be unresponsive to the usual doses of epinephrine used to treat allergic reaction. (7.2)
- CYP2D6 Inhibitors are likely to increase metoprolol concentration. (7.3)
- Concomitant use of glycosides, clonidine, and diltiazem and verapamil with beta-blockers can increase the risk of bradycardia. (7.4)
- Beta-blockers including metoprolol, may exacerbate the rebound hypertension that can follow the withdrawal of clonidine. (7.4)

8 USE IN SPECIFIC POPULATIONS

- Hepatic Impairment: Consider initiating metoprolol tartrate therapy at low doses while monitoring closely for adverse events. (8.6)

FULL PRESCRIBING INFORMATION

1 INDICATIONS AND USAGE

Metoprolol tartrate injection is indicated in the treatment of definite or suspected acute myocardial infarction in hemodynamically stable patients to reduce cardiovascular mortality when used in conjunction with oral metoprolol maintenance therapy.

2 DOSAGE AND ADMINISTRATION

Parenteral drug products should be inspected visually for particulate matter and discoloration prior to administration, whenever solution and container permit.

Initiate treatment in a coronary care or similar unit immediately after the patient's hemodynamic condition has stabilized.

Begin treatment in this early phase with the intravenous administration of three bolus injections of 5 mg of metoprolol tartrate injection each; give the injections at approximately 2-minute intervals. During the intravenous administration of metoprolol tartrate injection, monitor blood pressure, heart rate, and electrocardiogram.

Transition to Oral Metoprolol:

Following administration of metoprolol tartrate injection, transition patients to an oral formulation of metoprolol. See prescribing information for oral metoprolol for dose selection.

3 DOSAGE FORMS AND STRENGTHS

Injection: 5 mg metoprolol tartrate as a clear liquid supplied in 5 mL clear vials

4 CONTRAINDICATIONS

Hypersensitivity to metoprolol tartrate injection and related derivatives, or to any of the excipients; hypersensitivity to other beta blockers (cross sensitivity between beta blockers can occur).

Metoprolol tartrate injection is contraindicated in patients with a heart rate <45 beats/min; second-and third-degree heart block (unless a functioning pacemaker is present); significant first-degree heart block (P-R interval ≥0.24 sec); systolic blood pressure <100 mmHg; or decompensated cardiac failure.

5 WARNINGS AND PRECAUTIONS

5.1 Bradycardia

Bradycardia, including sinus pause, heart block, and cardiac arrest have occurred with the use of metoprolol tartrate injection. Patients with first-degree atrioventricular block, sinus node dysfunction, or conduction disorders may be at increased risk. Monitor heart rate and rhythm in patients receiving metoprolol tartrate injection. If severe bradycardia develops, reduce or stop metoprolol tartrate injection.

5.2 Heart Failure

Worsening cardiac failure may occur during metoprolol use. If such symptoms occur, increase diuretics and restore clinical stability before administering the next dose of metoprolol [see Dosage and Administration (2)]. Such episodes do not preclude subsequent successful titration of oral metoprolol.

5.3 Bronchospastic Disease

PATIENTS WITH BRONCHOSPASTIC DISEASES, IN GENERAL, SHOULD NOT RECEIVE BETA-BLOCKERS because they can exacerbate bronchospasm. Because of its relative beta1 cardio-selectivity, however, metoprolol may be used in patients with bronchospastic disease for initial treatment of myocardial infarction. Bronchodilators, including beta2-agonists, should be readily available or administered concomitantly [see Dosage and Administration (2)].

5.4 Pheochromocytoma

If metoprolol tartrate is used in the setting of pheochromocytoma, it should be given in combination with an alpha blocker, and only after the alpha blocker has been initiated. Administration of beta-blockers alone in the setting of pheochromocytoma has been associated with a paradoxical increase in blood pressure due to the attenuation of beta-mediated vasodilatation in skeletal muscle.

5.5 Hypoglycemia

Beta‐blockers may prevent early warning signs of hypoglycemia, such as tachycardia, and increase the risk for severe or prolonged hypoglycemia at any time during treatment, especially in patients with diabetes mellitus or children and patients who are fasting (i.e., surgery, not eating regularly, or are vomiting). If severe hypoglycemia occurs, patients should be instructed to seek emergency treatment.

5.6 Peripheral Vascular Disease

Beta-blockers can precipitate or aggravate symptoms of arterial insufficiency in patients with peripheral vascular disease.

6 ADVERSE REACTIONS

The following adverse reactions are described elsewhere in labeling:

- Worsening angina or myocardial infarction [see Warnings and Precautions (5)]
- Worsening heart failure [see Warnings and Precautions (5)]
- Worsening AV block [see Contraindications (4)]

6.1 Clinical Trials Experience

Because clinical trials are conducted under widely varying conditions, adverse reaction rates observed in the clinical trials of a drug cannot be directly compared to rates in the clinical trials of another drug and may not reflect the rates observed in practice. The adverse reaction information from clinical trials does, however, provide a basis for identifying the adverse events that appear to be related to drug use and for approximating rates.

Myocardial Infarction

These adverse reactions were reported from treatment regimens where intravenous metoprolol tartrate injection was administered, when tolerated.

Central Nervous System: Tiredness has been reported in about 1 of 100 patients. Vertigo, sleep disturbances, hallucinations, headache, dizziness, visual disturbances, confusion, and reduced libido have also been reported, but a drug relationship is not clear.

Cardiovascular: In a randomized comparison of metoprolol tartrate injection and placebo, the following adverse reactions were reported:

 | Metoprolol Tartrate | Placebo
Hypotension (systolic BP <90 mmHg) | 27.4% | 23.2%
Bradycardia (heart rate <40 beats/min) | 15.9% | 6.7%
Second- or third-degree heart block | 4.7% | 4.7%
First-degree heart block (P-R ≥0.26 sec) | 5.3% | 1.9%
Heart failure | 27.5% | 29.6%

Respiratory: Dyspnea of pulmonary origin has been reported in fewer than 1 of 100 patients.

Gastrointestinal: Nausea and abdominal pain have been reported in fewer than 1 of 100 patients.

Miscellaneous: Unstable diabetes and claudication have been reported.

6.2 Post-Marketing Experience

The following adverse reactions have been identified during post-approval use of metoprolol. Because these reactions are reported voluntarily from a population of uncertain size, it is not always possible to reliably estimate their frequency or establish a causal relationship to drug exposure.

Cardiovascular: Cold extremities, arterial insufficiency (usually of the Raynaud type), palpitations, peripheral edema, syncope, and hypotension.

Respiratory: Wheezing (bronchospasm), dyspnea.

Central Nervous System: Confusion, short-term memory loss, headache, nightmares, insomnia, nervousness, hallucinations.

Gastrointestinal: Nausea, dry mouth, constipation, flatulence, heartburn, hepatitis, vomiting.

Hypersensitive Reactions: Pruritus.

Miscellaneous: Musculoskeletal pain, arthritis, blurred vision, decreased libido, tinnitus, reversible alopecia, agranulocytosis, dry eyes, worsening of psoriasis, Peyronie's disease, photosensitivity.

7 DRUG INTERACTIONS

7.1 Catecholamine Depleting Drugs and Monoamine Oxidate (MAO) Inhibitors

Catecholamine depleting drugs (e.g., reserpine) and monoamine oxidase (MAO) inhibitors) may have an additive effect when given with beta-blocking agents. Observe patients treated with metoprolol plus a catecholamine depletor for evidence of hypotension or marked bradycardia, which may produce vertigo, syncope, or postural hypotension.

7.2 Epinephrine

While taking beta-blockers, patients with a history of severe anaphylactic reactions to a variety of allergens may be more reactive to repeated challenge and may be unresponsive to the usual doses of epinephrine used to treat an allergic reaction.

7.3 CYP2D6 Inhibitors

Drugs that are strong inhibitors of CYP2D6, such as quinidine, fluoxetine, paroxetine, and propafenone, were shown to double metoprolol concentrations. While there is no information about moderate or weak inhibitors, these too are likely to increase metoprolol concentration. Increases in plasma concentration decrease the cardioselectivity of metoprolol [see Clinical Pharmacology (12.3)]. Monitor patients closely, when the combination cannot be avoided.

7.4 Digitalis, Clonidine, and Calcium Channel Blockers and Other Drugs that Decrease Heart Rate

Digitalis glycosides, clonidine, diltiazem and verapamil slow atrioventricular conduction and decrease heart rate. Concomitant administration of beta-blockers with these and other drugs known to decrease heart rate such as sphingosine-1-phosphate receptor modulators (e.g. fingolimod) may result in additive heart rate lowering effects.

If clonidine and metoprolol are coadministered, withdraw the metoprolol several days before the gradual withdrawal of clonidine because beta-blockers may exacerbate the rebound hypertension that can follow the withdrawal of clonidine. If replacing clonidine by beta-blocker therapy, delay the introduction of beta-blockers for several days after clonidine administration has stopped.

7.5 Drugs that Decrease Blood Pressure

Concomitant administration of beta-blockers with other drugs known to decrease blood pressure may result in an enhanced hypotensive effect.

8 USE IN SPECIFIC POPULATIONS

8.1 Pregnancy

Risk Summary

Available data from published observational studies have not demonstrated an association of adverse developmental outcomes with maternal use of metoprolol during pregnancy (see Data). Untreated hypertension and heart failure during pregnancy can lead to adverse outcomes for the mother and the fetus (see Clinical Considerations). In animal reproduction studies, metoprolol has been shown to increase post-implantation loss and decrease neonatal survival in rats at oral dosages of 500 mg/kg/day, approximately 24 times the daily dose of 200 mg in a 60-kg patient on a mg/m^2 basis.

All pregnancies have a background risk of birth defect, loss, or other adverse outcomes. The estimated background risk of major birth defects and miscarriage for the indicated population is unknown. In the U.S. general population, the estimated background risk of major birth defects and miscarriage in clinically recognized pregnancies is 2 to 4% and 15 to 20%, respectively.

Clinical consideration

Disease-associated maternal and/or embryo/fetal risk

Hypertension in pregnancy increases the maternal risk for pre-eclampsia, gestational diabetes, premature delivery, and delivery complications (e.g., need for cesarean section, and post-partum hemorrhage). Hypertension increases the fetal risk for intrauterine growth restriction and intrauterine death. Pregnant women with hypertension should be carefully monitored and managed accordingly.

Stroke volume and heart rate increase during pregnancy, increasing cardiac output, especially during the first trimester. There is a risk for preterm birth with pregnant women with chronic heart failure in 3rd trimester of pregnancy.

Fetal/Neonatal adverse reactions

Metoprolol crosses the placenta. Neonates born to mothers who are receiving metoprolol during pregnancy, may be at risk for hypotension, hypoglycemia, bradycardia, and respiratory depression. Observe neonates for symptoms of hypotension, bradycardia, hypoglycemia and respiratory depression and manage accordingly.

Data

Human Data

Data from published observational studies did not demonstrate an association of major congenital malformations and use of metoprolol in pregnancy. The published literature has reported inconsistent findings of intrauterine growth retardation, preterm birth and perinatal mortality with maternal use of metoprolol during pregnancy; however, these studies have methodological limitations hindering interpretation. Methodological limitations include retrospective design, concomitant use of other medications, and other unadjusted confounders that may account for the study findings including the underlying disease in the mother. These observational studies cannot definitely establish or exclude any drug-associated risk during pregnancy.

Animal Data

Metoprolol has been shown to increase post-implantation loss and decrease neonatal survival in rats at oral dosages of 500 mg/kg/day, i.e. 24 times, on a mg/m^2 basis, the daily dose of 200 mg in a 60-kg patient.

No fetal abnormalities were observed when pregnant rats received metoprolol orally up to a dose of 200 mg/kg/day, i.e. 10 times, the daily dose of 200 mg in a 60-kg patient.

8.2 Lactation

Risk Summary

Limited available data from published literature report that metoprolol is present in human milk. The estimated daily infant dose of metoprolol received from breastmilk range from 0.05 mg to less than 1 mg. The estimated relative infant dosage was 0.5% to 2% of the mother's weight-adjusted dosage (see Data). No adverse reactions of metoprolol on the breastfed infant have been identified. There is no information regarding the effects of metoprolol on milk production.

Clinical consideration

Monitoring for adverse reactions

For a lactating woman who is a slow metabolizer of metoprolol, monitor the breastfed infant for bradycardia and other symptoms of beta blockade such as dry mouth, skin or eyes, diarrhea or constipation. In a report of 6 mothers taking metoprolol, none reported adverse effects in her breastfed infant.

Data

Limited published cases estimate the infant daily dose of metoprolol received from breast milk range from 0.05 mg to less than 1 mg.

In 2 women who were taking unspecified amount of metoprolol, milk samples were taken after one dose of metoprolol. The estimated amount of metoprolol and alpha-hydroxymetoprolol in breast milk is reported to be less than 2% of the mother's weight-adjusted dosage.

In a small study, breast milk was collected every 2 to 3 hours over one dosage interval, in three mothers (at least 3 months postpartum) who took metoprolol of unspecified amount. The average amount of metoprolol present in breast milk was 71.5 mcg/day (range 17.0 to 158.7). The average relative infant dosage was 0.5% of the mother's weight-adjusted dosage.

8.3 Females and Males of Reproductive Potential

Risk Summary

Based on the published literature, beta blockers (including metoprolol) may cause erectile dysfunction and inhibit sperm motility. In animal fertility studies, metoprolol has been associated with reversible adverse effects on spermatogenesis starting at oral dose level of 3.5 mg/kg in rats, which would correspond to a dose of 34 mg/day in humans in mg/m^2 equivalent, although other studies have shown no effect of metoprolol on reproductive performance in male rats.

No evidence of impaired fertility due to metoprolol was observed in rats [see Nonclinical Toxicology (13.1)].

8.4 Pediatric Use

Safety and effectiveness in pediatric patients have not been established.

8.5 Geriatric Use

In worldwide clinical trials of metoprolol tartrate injection in myocardial infarction, where approximately 478 patients were over 65 years of age (0 over 75 years of age), no age-related differences in safety and effectiveness were found. Other reported clinical experience in myocardial infarction has not identified differences in response between the elderly and younger patients. However, greater sensitivity of some elderly individuals taking metoprolol tartrate injection cannot be categorically ruled out. Therefore, in general, it is recommended that dosing proceed with caution in this population.

8.6 Hepatic Impairment

No studies have been performed with metoprolol in patients with hepatic impairment. Because metoprolol is metabolized by the liver, metoprolol blood levels are likely to increase substantially with poor hepatic function. Therefore, initiate therapy at doses lower than those recommended for a given indication.

10 OVERDOSAGE

Signs and Symptoms - Overdosage of metoprolol may lead to severe bradycardia, hypotension, and cardiogenic shock. Clinical presentation can also include: atrioventricular block, heart failure, bronchospasm, hypoxia, impairment of consciousness/coma, nausea and vomiting.

Treatment – Consider treating the patient with intensive care. Patients with myocardial infarction or heart failure may be prone to significant hemodynamic instability. Beta-blocker overdose may result in significant resistance to resuscitation with adrenergic agents, including beta-agonists. On the basis of the pharmacologic actions of metoprolol, employ the following measures.

Hemodialysis is unlikely to make a useful contribution to metoprolol elimination [see Clinical Pharmacology (12.3)].

Bradycardia: Evaluate the need for atropine, adrenergic-stimulating drugs or pacemaker to treat bradycardia and conduction disorders.

Hypotension: Treat underlying bradycardia. Consider intravenous vasopressor infusion, such as dopamine or norepinephrine.

Heart failure and shock: May be treated when appropriate with suitable volume expansion, injection of glucagon (if necessary, followed by an intravenous infusion of glucagon), intravenous administration of adrenergic drugs such as dobutamine, with α1 receptor agonistic drugs added in presence of vasodilation.

Bronchospasm: Can usually be reversed by bronchodilators.

11 DESCRIPTION

Metoprolol Tartrate Injection, USP, is a selective beta1-adrenoreceptor blocking agent, available in 5-mL vials for intravenous administration. Each vial contains a sterile solution of metoprolol tartrate USP, 5 mg, and sodium chloride USP, 45 mg, and water for injection USP. Metoprolol tartrate USP is (±)-1-(Isopropylamino)-3-[p-(2- methoxyethyl)phenoxy]-2-propanol L-(+)-tartrate (2:1) salt, and its structural formula is:

Metoprolol tartrate USP is a white, practically odorless, crystalline powder with a molecular weight of 684.82. It is very soluble in water; freely soluble in methylene chloride, in chloroform, and in alcohol; slightly soluble in acetone; and insoluble in ether.

12 CLINICAL PHARMACOLOGY

12.1 Mechanism of Action

Metoprolol is a beta1-selective (cardioselective) adrenergic receptor blocking agent. This preferential effect is not absolute, however, and at higher plasma concentrations, metoprolol also inhibits beta2-adrenoreceptors, chiefly located in the bronchial and vascular musculature.

Metoprolol has no intrinsic sympathomimetic activity, and membrane-stabilizing activity is detectable only at plasma concentrations much greater than required for beta-blockade. Animal and human experiments indicate that metoprolol slows the sinus rate and decreases AV nodal conduction.

The relative beta1-selectivity of metoprolol has been confirmed by the following: (1) In normal subjects, metoprolol is unable to reverse the beta2-mediated vasodilating effects of epinephrine. This contrasts with the effect of nonselective beta-blockers, which completely reverse the vasodilating effects of epinephrine. (2) In asthmatic patients, metoprolol reduces FEV1 and FVC significantly less than a nonselective beta-blocker, propranolol, at equivalent beta1-receptor blocking doses.

The precise mechanism of action of metoprolol tartrate injection in patients with suspected or definite myocardial infarction is not known.

12.2 Pharmacodynamics

When the drug was infused over a 10-minute period, in normal volunteers, maximum beta blockade was achieved at approximately 20 minutes. Equivalent maximal beta-blocking effect is achieved with oral and intravenous doses in the ratio of approximately 2.5:1. There is a linear relationship between the log of plasma levels and reduction of exercise heart rate.

In several studies of patients with acute myocardial infarction, intravenous followed by oral administration of metoprolol tartrate injection caused a reduction in heart rate, systolic blood pressure and cardiac output. Stroke volume, diastolic blood pressure and pulmonary artery end diastolic pressure remained unchanged.

12.3 Pharmacokinetics

Distribution

About 12% of the drug is bound to human serum albumin.

Metoprolol crosses the blood-brain barrier and has been reported in the CSF in a concentration 78% of the simultaneous plasma concentration.

Elimination

Elimination is mainly by biotransformation in the liver, and the plasma half-life ranges from approximately 3 to 7 hours.

Metabolism

Metoprolol is a racemic mixture of R- and S- enantiomers, and is primarily metabolized by CYP2D6. When administered orally, it exhibits stereoselective metabolism that is dependent on oxidation phenotype.

Excretion

Less than 5% of an oral dose of metoprolol is recovered unchanged in the urine; the rest is excreted by the kidneys as metabolites that appear to have no beta-blocking activity.

Following intravenous administration of metoprolol, the urinary recovery of unchanged drug is approximately 10%.

Mean dialytic clearance of metoprolol following oral administration in patients receiving high-flux hemodialysis is 87 mL/min. Mean total systemic clearance of metoprolol following intravenous administration in patients with chronic renal failure is 1 L/min.

Drug Interactions

CYP2D6

Metoprolol is metabolized predominantly by CYP2D6. In healthy subjects with CYP2D6 extensive metabolizer phenotype, coadministration of quinidine 100 mg, a potent CYP2D6 inhibitor, and immediate-release metoprolol 200 mg tripled the concentration of S-metoprolol and doubled the metoprolol elimination half-life. In four patients with cardiovascular disease, coadministration of propafenone 150 mg t.i.d. with immediate-release metoprolol 50 mg t.i.d. resulted in steady-state concentration of metoprolol 2- to 5-fold what is seen with metoprolol alone. Extensive metabolizers who concomitantly use CYP2D6 inhibiting drugs will have increased (several-fold) metoprolol blood levels, decreasing metoprolol's cardioselectivity [see Drug Interactions (7.2)].

12.5 Pharmacogenomics

CYP2D6 is absent in about 8% of Caucasians (poor metabolizers) and about 2% of most other populations. CYP2D6 can be inhibited by several drugs. Poor metabolizers of CYP2D6 will have increased (several-fold) metoprolol blood levels, decreasing metoprolol's cardioselectivity.

13 NONCLINICAL TOXICOLOGY

13.1 Carcinogenesis, Mutagenesis, Impairment of Fertility

Long-term studies in animals have been conducted to evaluate the carcinogenic potential of metoprolol tartrate. In 2-year studies in rats at three oral dosage levels of up to 800 mg/kg/day (39 times, on a mg/m^2 basis, the daily dose of 200 mg for a 60 kg patient), there was no increase in the development of spontaneously occurring benign or malignant neoplasms of any type. The only histologic changes that appeared to be drug related were an increased incidence of generally mild focal accumulation of foamy macrophages in pulmonary alveoli and a slight increase in biliary hyperplasia. In a 21-month study in Swiss albino mice at three oral dosage levels of up to 750 mg/kg/day (18 times, on a mg/m^2 basis, the daily dose of 200 mg for a 60- kg patient), benign lung tumors (small adenomas) occurred more frequently in female mice receiving the highest dose than in untreated control animals. There was no increase in malignant or total (benign plus malignant) lung tumors, nor in the overall incidence of tumors or malignant tumors. This 21-month study was repeated in CD-1 mice, and no statistically or biologically significant differences were observed between treated and control mice of either sex for any type of tumor.

All genotoxicity tests performed on metoprolol tartrate (a dominant lethal study in mice, chromosome studies in somatic cells, a Salmonella/mammalian-microsome mutagenicity test, and a nucleus anomaly test in somatic interphase nuclei) and metoprolol succinate (a Salmonella/mammalian-microsome mutagenicity test) were negative.

No evidence of impaired fertility due to metoprolol tartrate was observed in a study performed in rats at doses up to 24 times, on a mg/m^2 basis, the daily dose of 200 mg in a 60-kg patient.

14 CLINICAL STUDIES

In a large (1,395 patients randomized), double-blind, placebo-controlled clinical study, metoprolol tartrate injection was shown to reduce 3-month mortality by 36% in patients with suspected or definite myocardial infarction.

Patients were randomized and treated as soon as possible after their arrival in the hospital, once their clinical condition had stabilized and their hemodynamic status had been carefully evaluated. Subjects were ineligible if they had hypotension, bradycardia, peripheral signs of shock, and/or more than minimal basal rales as signs of congestive heart failure. Initial treatment consisted of intravenous followed by oral administration of metoprolol tartrate injection or placebo, given in a coronary care or comparable unit. Oral maintenance therapy with metoprolol tartrate injection or placebo was then continued for 3 months. After this double-blind period, all patients were given metoprolol tartrate injection and followed up to 1 year.

The median delay from the onset of symptoms to the initiation of therapy was 8 hours in both the metoprolol tartrate injection - and placebo-treatment groups. Among patients treated with metoprolol tartrate injection, there were comparable reductions in 3-month mortality for those treated early (≤8 hours) and those in whom treatment was started later. Significant reductions in the incidence of ventricular fibrillation and in chest pain following initial intravenous therapy were also observed with metoprolol tartrate injection and were independent of the interval between onset of symptoms and initiation of therapy.

In this study, patients treated with metoprolol received the drug both very early (intravenously) and during a subsequent 3-month period, while placebo patients received no beta-blocker treatment for this period. The study thus was able to show a benefit from the overall metoprolol regimen but cannot separate the benefit of very early intravenous treatment from the benefit of later beta-blocker therapy. Nonetheless, because the overall regimen showed a clear beneficial effect on survival without evidence of an early adverse effect on survival, one acceptable dosage regimen is the precise regimen used in the trial. Because the specific benefit of very early treatment remains to be defined however, it is also reasonable to administer the drug orally to patients at a later time as is recommended for certain other beta blockers.

16 HOW SUPPLIED/STORAGE AND HANDLING

Metoprolol Tartrate Injection, USP is available as 5 mL vials, each containing 5 mg of metoprolol tartrate:

Product Code | Unit of Sale | Strength | Each
606005 | NDC 63323-660-05 Unit of 10 | 5 mg/5 mL (1 mg/mL) | NDC 63323-660-01 5 mL Single-Dose Vial
RF606005 | NDC 65219-665-05 Unit of 10 | 5 mg/5 mL (1 mg/mL) | NDC 65219-665-01 5 mL Single-Dose Vial This product is RFID-enabled.

Store at 20°C to 25°C (68°F to 77°F) [see USP Controlled Room Temperature].

Do not freeze. Protect from light.

Retain in carton until time of use.

The container closure is not made with natural rubber latex.

17 PATIENT COUNSELING INFORMATION

Advise patients (1) to avoid operating automobiles and machinery or engaging in other tasks requiring alertness until the patient's response to therapy with metoprolol tartrate injection has been determined; (2) to contact the physician if any difficulty in breathing occurs; (3) to inform the physician or dentist before any type of surgery that he or she is taking metoprolol tartrate injection.

Risk of Hypoglycemia

Inform patients or caregivers that there is a risk of hypoglycemia when metoprolol tartrate injection is given to patients who are fasting or who are vomiting. Monitor for signs of hypoglycemia [see Warnings and Precautions (5.5)].

Lake Zurich, IL 60047
www.fresenius-kabi.com/us

451161C

PACKAGE LABEL

PACKAGE LABEL – PRINCIPAL DISPLAY – Metoprolol 5 mL Single Dose Vial Label

NDC 65219-665-01 RF606005

METOPROLOL TARTRATE INJECTION, USP

5 mg/5 mL (1 mg/mL)

For Intravenous Use

Rx only

5 mL Single - Dose Vial

PACKAGE LABEL

PACKAGE LABEL – PRINCIPAL DISPLAY – Metoprolol 5 mL Single Dose Tray Label

NDC 65219-665-05 RF606005

METOPROLOL TARTRATE INJECTION, USP

5 mg/5 mL (1 mg/mL)

For Intravenous Use

Rx only

10 x 5 mL Single – Dose Vials